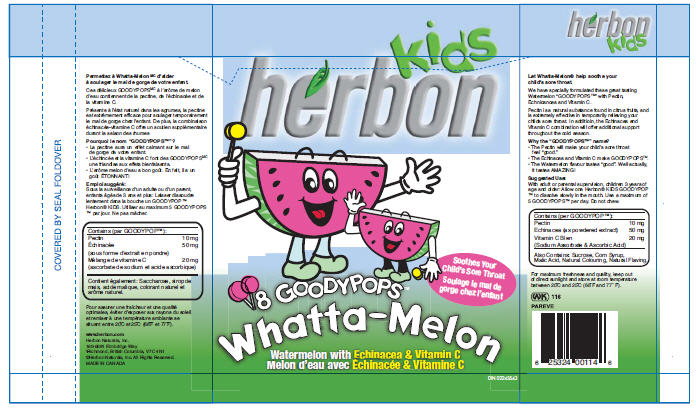 DRUG LABEL: Herbon Berry Buddies/Watermelon Goodypops
NDC: 44597-5605 | Form: LOZENGE
Manufacturer: Purity Life Division of SunOpta
Category: otc | Type: HUMAN OTC DRUG LABEL
Date: 20091015

ACTIVE INGREDIENTS: Pectin 10 mg/1 1; Echinacea Purpurea 50 mg/1 1
INACTIVE INGREDIENTS: Sucrose 4312 mg/1 1; Corn Syrup; Malic Acid; Ascorbic Acid; Sodium Ascorbate

INDICATIONS AND USAGE

Let Whatta-Melon® help soothe your child's sore throat.

We have specially formulated these great tasting Watermelon "GOODYPOPS™" with Pectin, Echnicancea and Vitamin C.

Pectin is a natural substance found in citrus fruits, and is extremely effective in temporarily relieving your childs sore throat. In additioin, the Echinacea and Vitamin C combination will offer additional support throughout the cold season.

Why the "GOODYPOPS™" name?

- The Pectin will make your child's sore throat feel "good."
- The Echinacea and Vitamin C make GOODYPOPS™.
- The Watermelon flavour tastes "good". Well actually, it tastes AMAZING!

Suggested Use:

With adult or parental supervision, children 3 years of age and older: Allow one Herbon® KIDS GOODYPOP ™ to dissolve slowly in the mouth. Use a maximum of 5 GOODYPOPS™ per day. Do not chew.

ACTIVE INGREDIENT

Contains (per GOODYPOP™):
Pectin | 10 mg
Echinacea (as powdered extract) | 50 mg
Vitamin C Blen (Sodium Assorbate & Ascorbic Acid) | 20 mg
Also Contains: Sucrose, Corn Syrup, Malic Acid, Natural Colouring, Natural Flaving.

STORAGE AND HANDLING

For maximum freshness and quality, keep out of direct sunlight and store at room temperature between 20°C and 25°C (68°F and 77° F).

PRINCIPAL DISPLAY PANEL - 8 Lozenge Bag

herbon Kids

8 GOODYPOPS™

Whatta-Melon

Soothes Your
Child's Sore Throat

Watermelon with Echinacea & Vitamin C